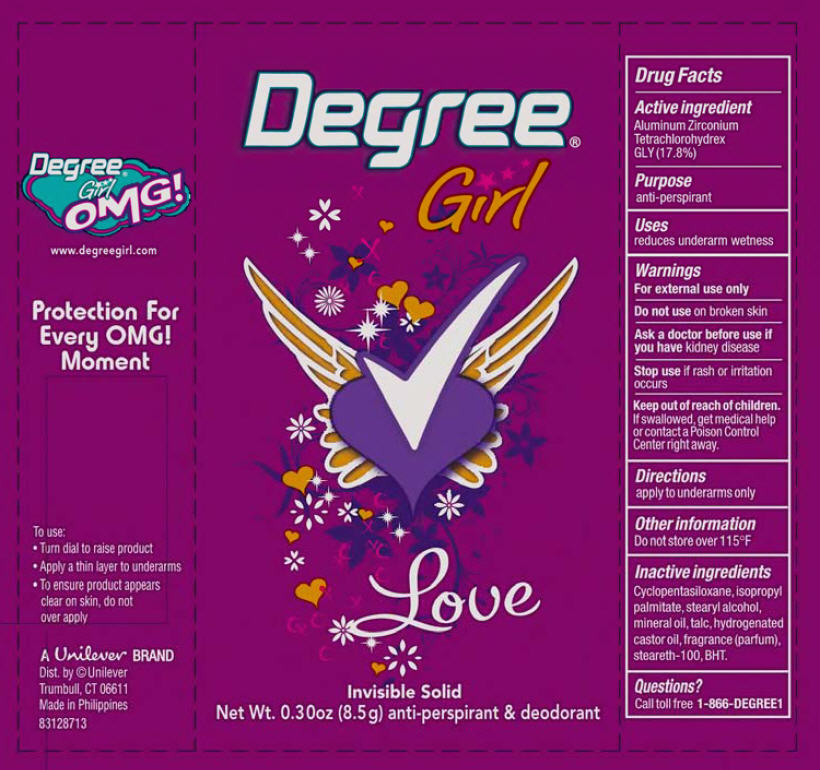 DRUG LABEL: Degree
NDC: 64942-1155 | Form: STICK
Manufacturer: Conopco Inc. d/b/a Unilever
Category: otc | Type: HUMAN OTC DRUG LABEL
Date: 20110106

ACTIVE INGREDIENTS: Aluminum Zirconium Tetrachlorohydrex GLY 17.8 g/100 g
INACTIVE INGREDIENTS: CYCLOMETHICONE 5; ISOPROPYL PALMITATE; Stearyl Alcohol; HYDROGENATED CASTOR OIL; TALC; BUTYLATED HYDROXYTOLUENE; MINERAL OIL; STEARETH-100

Degree Girl Love antiperspirant deodorant

Active Ingredient

Aluminum Zirconium Tetrachlorohydrex GLY (17.8%)

Purpose
anti-perspirant

INDICATIONS AND USAGE

Uses · reduces underarm wetness

Warnings
For External Use Only

Do not use on broken skin

Ask a doctor before use if you have kidney disease

Stop use if rash or irritation occurs

Keep out of reach of children. If swallowed, get medical help or contact a Poison Control Center right away

DOSAGE AND ADMINISTRATION

To use:
· turn dial to raise product
· apply a thin layer to underarms
· to ensure product appears clear on skin, do not over apply

Inactive ingredients
Cyclopentasiloxane
Isopropyl Palmitate
Stearyl Alcohol
Mineral Oil
Talc
Hydrogenated Castor Oil
Fragrance (Parfum)
Steareth-100
BHT

Questions?
Call toll-free 1-866-DEGREE1

PACKAGE LABEL

PDP 0.30 oz